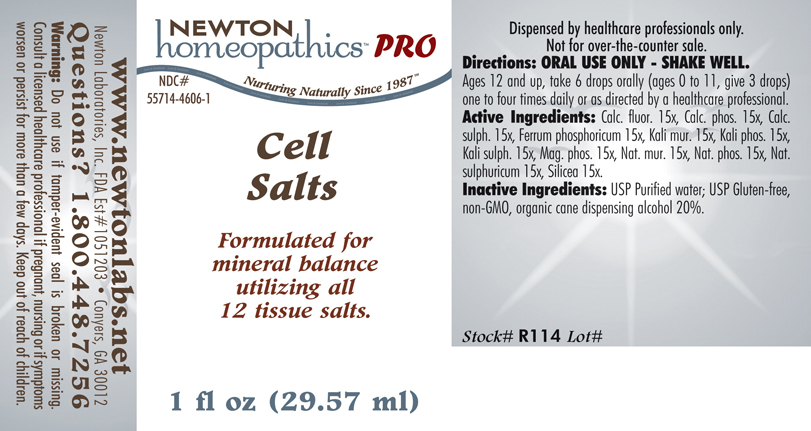 DRUG LABEL: Cell Salts 
NDC: 55714-4606 | Form: LIQUID
Manufacturer: Newton Laboratories, Inc.
Category: homeopathic | Type: HUMAN PRESCRIPTION DRUG LABEL
Date: 20110601

ACTIVE INGREDIENTS: Calcium Fluoride 15 [hp_X]/1 mL; Tribasic Calcium Phosphate 15 [hp_X]/1 mL; Calcium Sulfate Anhydrous 15 [hp_X]/1 mL; Ferric Phosphate 15 [hp_X]/1 mL; Potassium Chloride 15 [hp_X]/1 mL; Potassium Phosphate, Dibasic 15 [hp_X]/1 mL; Potassium Sulfate 15 [hp_X]/1 mL; Magnesium Phosphate, Dibasic Trihydrate 15 [hp_X]/1 mL; Sodium Chloride 15 [hp_X]/1 mL; Sodium Phosphate, Dibasic, Heptahydrate 15 [hp_X]/1 mL; Sodium Sulfate 15 [hp_X]/1 mL; Silicon Dioxide 15 [hp_X]/1 mL

Cell Salts

PRODUCT NAME & INDICATIONS SECTION

CELL SALTS Formulated for mineral balance utilizing all 12 tissue salts.

DIRECTION SECTION

Directions: ORAL USE ONLY - SHAKE WELL. Ages 12 and up, take 6 drops orally (ages 0 to 11, give 3 drops) one to four times daily or as directed by a healthcare professional.

ACTIVE INGREDIENT SECTION

Calc. fluor. 15x, Calc. phos. 15x, Calc. sulph. 15x, Ferrum phosphoricum 15x, Kali mur. 15x, Kali phos. 15x, Kali sulph. 15x, Mag. phos. 15x, Nat. mur. 15x, Nat. phos. 15x, Nat. sulphuricum 15x, Silicea 15x.

PURPOSE SECTION

Formulated for mineral balance utilizing all 12 tissue salts.

INACTIVE INGREDIENT SECTION

Inactive Ingredients:USP Purified Water; USP Gluten-free, non-GMO, organic cane dispensing alcohol 20%.

QUESTIONS? SECTION

www.newtonlabs.net Newton Laboratories, Inc. FDA Est # 1051203 -Conyers, GA 30012
Questions? 1.800.448.7256

WARNINGS SECTION

Warning: Do not use if tamper - evident seal is broken or missing. Consult a licensed healthcare professional if pregnant, nursing or if symptoms worsen or persist for more than a few days. Keep out of reach of children.

OTC - PREGNANCY OR BREAST FEEDING SECTION

Consult a licensed healthcare professional if pregnant or nursing or if symptoms worsen or persist for more than a few days.

OTC - KEEP OUT OF REACH OF CHILDREN SECTION

Keep out of reach of children.